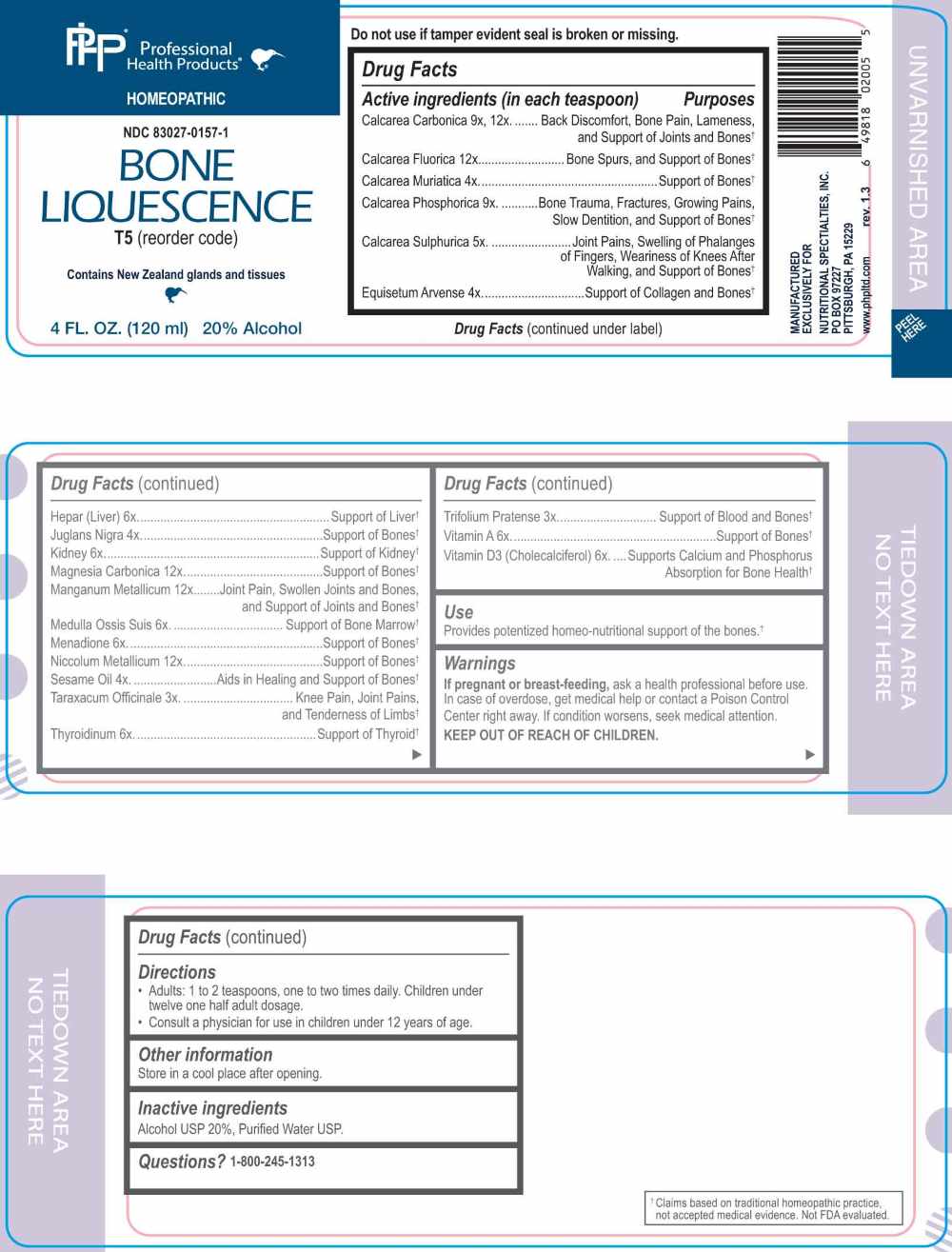 DRUG LABEL: Bone Liquescence
NDC: 83027-0157 | Form: LIQUID
Manufacturer: Nutritional Specialties, Inc.
Category: homeopathic | Type: HUMAN OTC DRUG LABEL
Date: 20251125

ACTIVE INGREDIENTS: TARAXACUM OFFICINALE 3 [hp_X]/1 mL; TRIFOLIUM PRATENSE FLOWER 3 [hp_X]/1 mL; CALCIUM CHLORIDE 4 [hp_X]/1 mL; EQUISETUM ARVENSE TOP 4 [hp_X]/1 mL; BLACK WALNUT HUSK 4 [hp_X]/1 mL; SESAME OIL 4 [hp_X]/1 mL; CALCIUM SULFATE ANHYDROUS 5 [hp_X]/1 mL; HEPARIN, BOVINE 6 [hp_X]/1 mL; BEEF KIDNEY 6 [hp_X]/1 mL; SUS SCROFA BONE MARROW 6 [hp_X]/1 mL; MENADIONE 6 [hp_X]/1 mL; THYROID, BOVINE 6 [hp_X]/1 mL; VITAMIN A 6 [hp_X]/1 mL; CHOLECALCIFEROL 6 [hp_X]/1 mL; TRIBASIC CALCIUM PHOSPHATE 9 [hp_X]/1 mL; OYSTER SHELL CALCIUM CARBONATE, CRUDE 9 [hp_X]/1 mL; CALCIUM FLUORIDE 12 [hp_X]/1 mL; MANGANESE 12 [hp_X]/1 mL; NICKEL 12 [hp_X]/1 mL; MAGNESIUM CARBONATE 12 [hp_X]/1 mL
INACTIVE INGREDIENTS: WATER; ALCOHOL

DRUG FACTS:

ACTIVE INGREDIENTS:

(in each teaspoon) Calcarea Carbonica 9X, 12X, Calcarea Fluorica 12X, Calcarea Muriatica 4X, Calcarea Phosphorica 9X, Calcarea Sulphurica 5X, Equisetum Arvense 4X, Hepar (Liver) 6X, Juglans Nigra 4X, Kidney 6X, Magnesia Carbonica 12X, Manganum Metallicum 12X, Medulla Ossis Suis 6X, Menadione 6X, Niccolum Metallicum 12X, Sesame Oil 4X, Taraxacum Officinale 3X, Thyroidinum 6X, Trifolium Pratense 3X, Vitamin A 6X, Vitamin D3 (Cholecalciferol) 6X.

PURPOSE:

Calcarea Carbonica – Back Discomfort, Bone Pain, Lameness, and Support of Joints and Bones,† Calcarea Fluorica – Bone Spurs, and Support of Bones,† Calcarea Muriatica – Support of Bones,† Calcarea Phosphorica – Bone Trauma, Fractures, Growing Pains, Slow Dentition, and Support of Bones,† Calcarea Sulphurica – Joint Pains, Swelling of Phalanges of Fingers, Weariness of Knees After Walking, and Support of Bones,† Equisetum Arvense – Support of Collagen and Bones,† Hepar (Liver) – Support of Liver,† Juglans Nigra – Support of Bones,† Kidney – Support of Kidneys,† Magnesia Carbonica – Support of Bones,† Manganum Metallicum – Joint Pain, Swollen Joints and Bones, and Support of Joints and Bones,† Medulla Ossis Suis – Support of Bone Marrow,† Menadione – Support of Bones,† Niccolum Metallicum – Support of Bones,† Sesame Oil – Aids in Healing and Support of Bones,† Taraxacum Officinale -Knee Pain, Joint Pains, and Tenderness of Limbs,† Thyroidinum – Support of Thyroid,† Trifolium Pratense – Support of Blood and Bones,† Vitamin A – Support of Bones,† Vitamin D3 (Cholecalciferol) – Supports Calcium and Phosphorus Absorption for Bone Health†

†Claims based on traditional homeopathic practice, not accepted medical evidence. Not FDA evaluated.

USE:

Provides potentized homeo-nutritional support of the bones.

†Claims based on traditional homeopathic practice, not accepted medical evidence. Not FDA evaluated.

WARNINGS:

If pregnant or breast-feeding, ask a health professional before use.

In case of overdose, get medical help or contact a Poison Control Center right away.

If condition worsens, seek medical attention.

KEEP OUT OF REACH OF CHILDREN

Do not use if tamper evident seal is broken or missing.

Store in a cool place after opening.

KEEP OUT OF REACH OF CHILDREN:

In case of overdose, get medical help or contact a Poison Control Center right away.

DIRECTIONS:

• Adults: 1 to 2 teaspoons, one to two times daily. Children under twelve one half adult dosage.

• Consult a physician for use in children under 12 years of age.

INACTIVE INGREDIENTS:

Alcohol USP 20%, Purified Water USP.

QUESTIONS:

MANUFACTURED EXCLUSIVELY FOR

NUTRITIONAL SPECIALTIES, INC.

PO BOX 97227

PITTSBURG, PA 15229

www.phpltd.com

1-800-245-1313

PACKAGE LABEL DISPLAY:

Professional

Health Products

HOMEOPATHIC

NDC 83027-0157-1

BONE LIQUESCENCE

4 FL. OZ (120 ml)